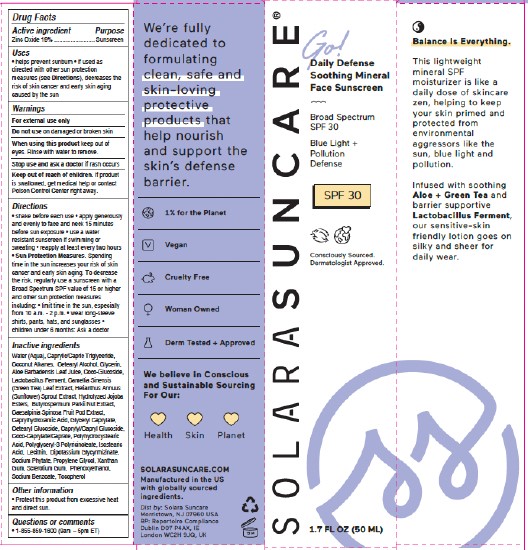 DRUG LABEL: Go Daily Defense Soothing Mineral Face Sunscreen

NDC: 73054-116 | Form: LOTION
Manufacturer: SOLARA SUNCARE, INC.
Category: otc | Type: HUMAN OTC DRUG LABEL
Date: 20251222

ACTIVE INGREDIENTS: ZINC OXIDE 19 g/100 mL
INACTIVE INGREDIENTS: MEDIUM-CHAIN TRIGLYCERIDES; COCONUT ALKANES; HELIANTHUS ANNUUS SPROUT; POLYGLYCERYL-3 PENTARICINOLEATE; ISOSTEARIC ACID; GLYCYRRHIZINATE DIPOTASSIUM; LIMOSILACTOBACILLUS FERMENTUM; SODIUM BENZOATE; CAPRYLYL/CAPRYL OLIGOGLUCOSIDE; LECITHIN, SOYBEAN; CAESALPINIA SPINOSA FRUIT POD; CAPRYLHYDROXAMIC ACID; PHYTATE SODIUM; WATER; GLYCERIN; CETYL ALCOHOL; TOCOPHEROL; COCO GLUCOSIDE; POLYHYDROXYSTEARIC ACID (2300 MW); PHENOXYETHANOL; ALOE VERA LEAF; HYDROLYZED JOJOBA ESTERS (ACID FORM); COCO-CAPRYLATE/CAPRATE; PROPYLENE GLYCOL; BETASIZOFIRAN; XANTHAN GUM; SHEANUT; GREEN TEA LEAF; GLYCERYL CAPRYLATE; CETEARYL GLUCOSIDE

SOLARA (as PLD) - Go! Daily Defense Soothing Mineral Face Sunscreen SPF-30 (73054-116)

ACTIVE INGREDIENTS

Zinc Oxide 19%

PURPOSE

Sunscreen

USES

- helps prevent sunburn
- if used as directed with other sun protection measures (see Directions), decreases the risk of skin cancer and early skin aging caused by the sun

Warnings

For external use only

Do not use on damaged or broken skin

When using this product keep out of eyes. Rinse with water to remove.

Stop use and ask a doctor if rash occurs

Keep out of reach of children. If product is swallowed, get medical help or contact Poison Control Center right away.

DIRECTIONS

- shake before each use
- apply generously and evenly to face and neck 15 minutes before sun exposure
- use a water resistant sunscreen if swimming or sweating
- reapply at least every 2 hours

- Sun Protection Measures. Spending time in the sun increases your risk of skin cancer and early skin aging. To decrease the risk, regularly use a sunscreen with a Broad Spectrum SPF value of 15 or higher and other sun protection measures including:
- limit time in the sun, especially from 10 a.m. - 2 p.m.
- wear long-sleeve shirts, pants, hats, and sunglasses
- children under 6 months: Ask a doctor

INACTIVE INGREDIENTS

Water (Aqua), Caprylic/Capric Triglyceride, Coconut Alkanes, Cetearyl Alcohol, Glycerin, Aloe Barbadensis Leaf Juice, Coco-Glucoside, Lactobacillus Ferment, Camellia Sinensis (Green Tea) Leaf Extract, Helianthus Annuus (Sunflower) Sprout Extract, Hydrolyzed Jojoba Esters, Butyrospermum Parkii Nut Extract, Caesalpinia Spinosa Fruit Pod Extract, Caprylhydroxamic Acid, Glyceryl Caprylate, Cetearyl Glucoside, Caprylyl/Capryl Glucoside, Coco-Caprylate/Caprate, Polyhydroxystearic Acid, Polyglyceryl-3 Polyricinoleate, Isostearic Acid, Lecithin, Dipotassium Glycyrrhizinate, Sodium Phytate, Propylene Glycol, Xanthan Gum, Sclerotium Gum, Phenoxyethanol, Sodium Benzoate, Tocopherol

OTHER INFORMATION

- Protect this product from excessive heat and direct sun.

QUESTIONS OR COMMENTS

- 1-855-859-1600 (9am – 5pm ET)